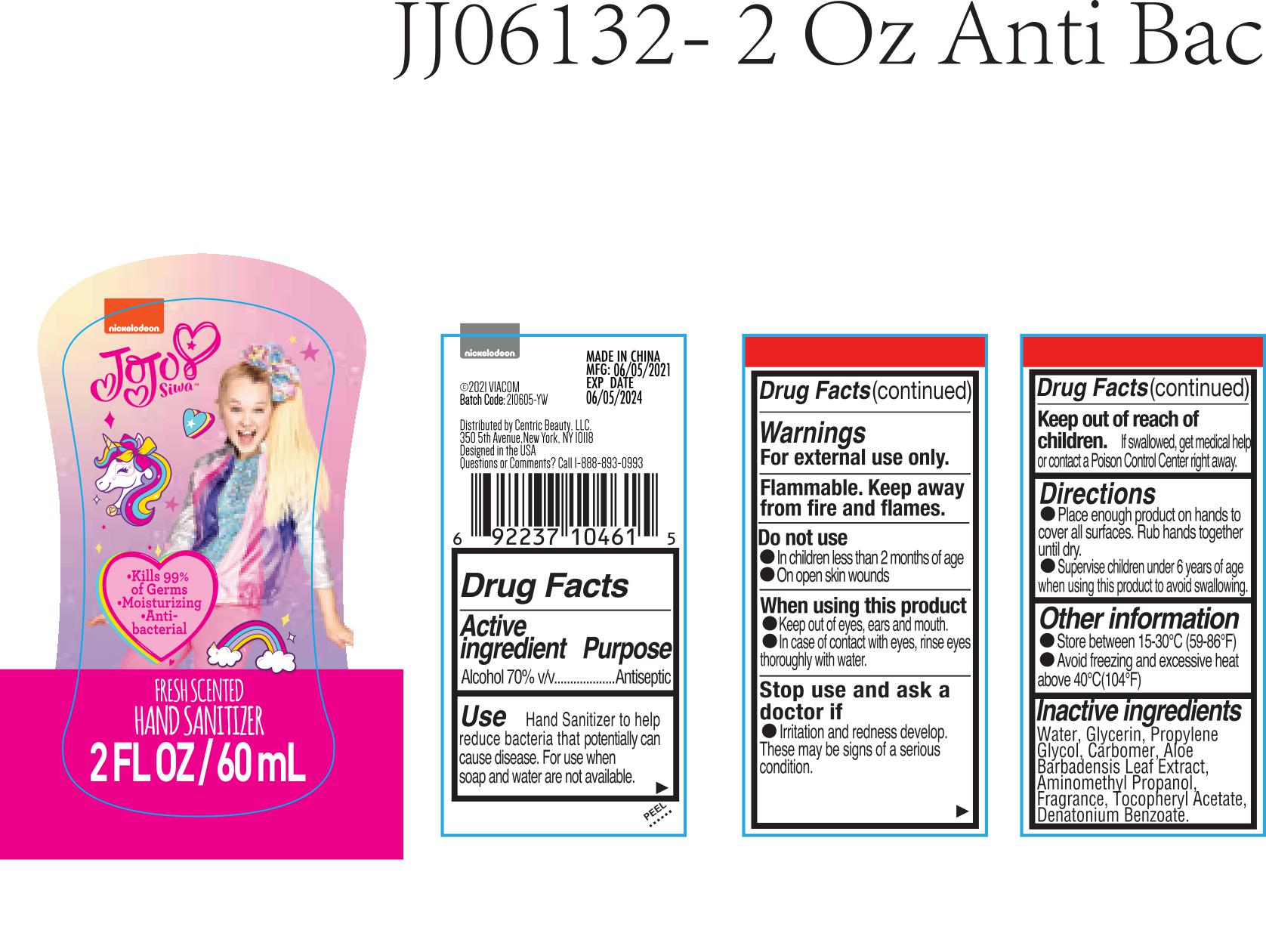 DRUG LABEL: JoJo Siwa Fresh Scented Hand Sanitizer
NDC: 54699-015 | Form: GEL
Manufacturer: Ouya Cosmetics Co., Ltd of Yiwu City
Category: otc | Type: HUMAN OTC DRUG LABEL
Date: 20210609

ACTIVE INGREDIENTS: ALCOHOL 70 mL/100 mL
INACTIVE INGREDIENTS: AMINOMETHYLPROPANOL; ALOE VERA LEAF; GLYCERIN; CARBOXYPOLYMETHYLENE; WATER; ALPHA-TOCOPHEROL ACETATE; DENATONIUM BENZOATE; PROPYLENE GLYCOL

JoJo Siwa Fresh Scented Hand Sanitizer

Questions or Comments?

Call 1-888-893-0993

Active Ingredient

Alcohol 70% v/v.

Purpose

Antiseptic

Use

Hand Sanitizer to help reduce bacteria that potentially can cause disease. For use when soap and water are not available.

Warnings

For external use only. Flammable. Keep away from fire and flames.

Do not use

- In children less than 2 months of age
- On open skin wounds

When using this product

Keep out of eyes, ears, and mouth. In case of contact with eyes, rinse eyes thoroughly with water.

Stop use and ask a doctor if

Irritation and redness develop. These may be signs of a serious condition.

Keep out of reach of children

If swallowed, get medical help or contact a Poison Control Center right away.

Directions

- Place enough product on hands to cover all surfaces. Rub hands together until dry.
- Supervise children under 6 years of age when using this product to avoid swallowing.

Other information

- Store between 15-30°C (59-86°F)
- Avoid freezing and excessive heat above 40°C (104°F)

Inactive ingredients

Water, Glycerin, Propylene Glycol, Carbomer, Aloe Barbadensis Leaf Extract, Aminomethyl Propanol, Fragrance, Tocopheryl Acetate, Denatonium Benzoate.